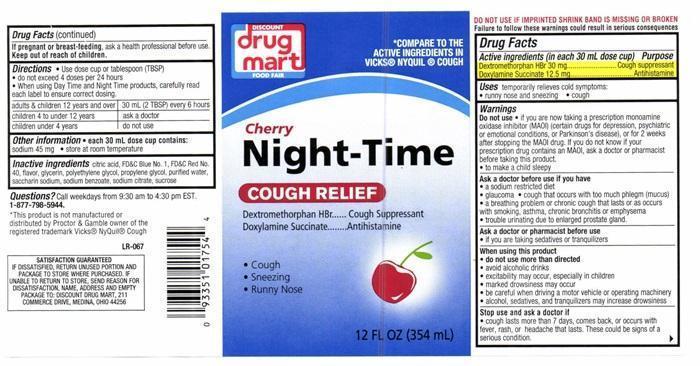 DRUG LABEL: Night-Time
NDC: 53943-508 | Form: LIQUID
Manufacturer: Discount Drug Mart
Category: otc | Type: HUMAN OTC DRUG LABEL
Date: 20251223

ACTIVE INGREDIENTS: DEXTROMETHORPHAN HYDROBROMIDE 30 mg/30 mL; DOXYLAMINE SUCCINATE 12.5 mg/30 mL
INACTIVE INGREDIENTS: ANHYDROUS CITRIC ACID; FD&C BLUE NO. 1; FD&C RED NO. 4; GLYCERIN; POLYETHYLENE GLYCOL, UNSPECIFIED; PROPYLENE GLYCOL; WATER; SACCHARIN SODIUM; SODIUM BENZOATE; SODIUM CITRATE; SUCROSE

Drug Facts Active ingredients (in each 30 mL dose cup)

Dextromethorphan HBr 30 mg

Doxylamine Succinate 12.5 mg

Purpose

Cough suppressant

Antihistamine

Keep out of reach of children

Uses

temporarily relieves cold symptoms:

- runny nose and sneezing
- cough

Warnings

DO NOT USE IF IMPRINTED SHRINK BRAND IS MISSING OR BROKEN

Failure to follow these warnings could result in serious consequences.

Do not use

- if you are now taking a prescription monamine oxidase inhibitor (MAOI) (certain drugs for depression psychiatric or emotional conditions, or Parkinson's disease), or for 2 weeks after stopping the MAOI drug. If you do not know if your prescription drug contains an MAOI, ask a doctor or pharmacist before taking this product.
- to make a child sleepy

Ask a doctor befor use if you have

- a sodium restricted diet
- glaucoma
- cough that occurs with too much phlegm (mucus)
- a breathing problem or chronic cough that lasts or as occurs with smoking, asthma, chronic bronchitis or emphysema
- trouble urinating due to enlarged prostate gland

Ask a doctor or pharmacist before use

- if you are taking sedatives or tranquilizers

When using this product

- do not use more than directed
- avoid alcoholic drinks
- excitability may occur, especially in children
- marked drowsiness may occur
- be careful when driving a motor vehicle or operating machinery
- alcohol, sedatives, and tranquilizers may increase drowsiness

Stop use and ask a doctor if

- cough lasts more than 7 days, comes back, or occurs with fever, rash, or headache that lasts. These could be signs of a serious condition.

If pregnant or breast feeding,

ask a health professionalbefore use.

Directions

- Use dose cup or tablespoon (TBSP)
- do not exceed 4 doses per 24 hours
- When using Day Time and Night Time products, carefully read each label to ensure

adults and children 12 years and over | 30 mL (2 TBSP) every 6 hours
children 4 to under 12 years | ask a doctor
children under 4 years | do not use

Other information

- each 30 mL dose cup contains: sodium 45 mg
- store at room temperature

Inactive ingredients

citric acid, FD and C Blue No. 1, FD and C Red No. 40, flavor, glycerin, polyethylene glycol, propylene glycol, purified water, saccharin sodium, sodium benzoate, sodium citrate, sucrose

Questions ?

Call weekdays from 9:30 am to 4:30 pm EST.

1-877-798-5944.

DISCOUNT drug mart FOOD FAIR Cherry Night-Time COUGH REFIEF product label

*COMPARE TO THE INGREDIENTS IN VICKS® NYQUIL® COUGH

DISCOUNT

drug mart

FOOD FAIR

Cherry

Night-Time

COUGH RELIEF

Dextromethorphan HBr ..... Cough Suppressant

Doxylamine Succiate ......... Antihistamine

- Cough
- Sneezing
- Runny Nose

12 FL OZ (354 mL)

* This product is not manufactured or distributed by Proctor and Gamble owner of the registered trademark Vicks® Nyquil® Cough

LR-067

SATISFACTION GUARANTEED

IF DISSATISFIED, RETURN UNUSED PORTION AND PACKAGE TO THE STORE WHERE PURCHASED. IF UNABLE TO RETURN TO THE STORE, SEND REASON FOR DISSATISFACTION , NAME, ADDRESS AND EMPTY PACKAGE TO: DISCOUNT DRUG MART, 211 COMMERCE DRIVE MEDINNA, OHIO 44256

res